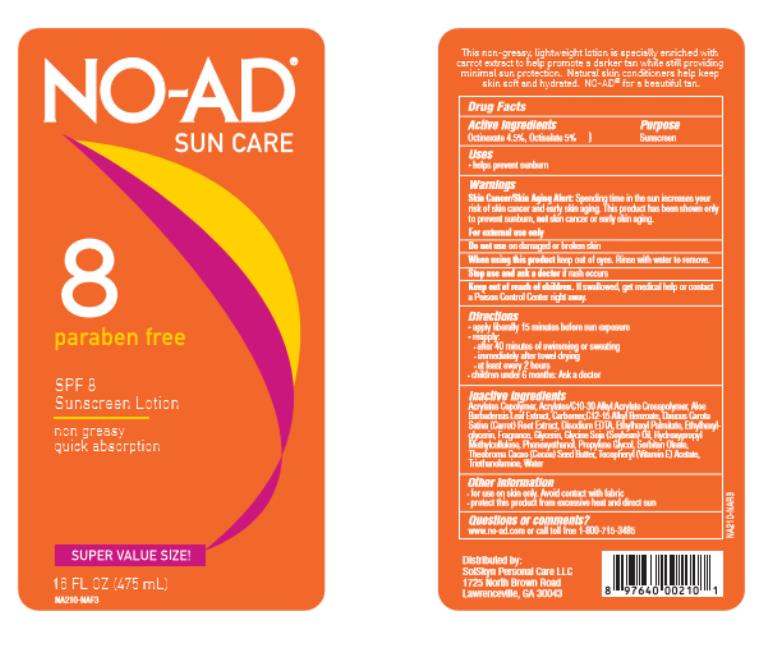 DRUG LABEL: NO-AD SPF 8 Tanning
NDC: 70281-100 | Form: LOTION
Manufacturer: SolSkyn Personal Care LLC
Category: otc | Type: HUMAN OTC DRUG LABEL
Date: 20180215

ACTIVE INGREDIENTS: OCTINOXATE 4.5 g/100 g; OCTISALATE 5 g/100 g
INACTIVE INGREDIENTS: CARBOMER INTERPOLYMER TYPE A (55000 CPS); ALOE VERA LEAF; ALKYL (C12-15) BENZOATE; CARROT; EDETATE DISODIUM ANHYDROUS; ETHYLHEXYL PALMITATE; ETHYLHEXYLGLYCERIN; GLYCERIN; SOYBEAN OIL; HYPROMELLOSE, UNSPECIFIED; PHENOXYETHANOL; PROPYLENE GLYCOL; SORBITAN MONOOLEATE; COCOA BUTTER; TROLAMINE; WATER

No-Ad SPF 8 Sunscreen Lotion

No Ad SPF8 Sunscreen Lotion

Active Ingredients

Octinoxate 4.5%, Octisalate 5%

Purpose

Sunscreen

Uses

- helps prevent sunburn

Warnings

Skin Cancer/Skin Aging Alert: Spending time in the sun increases your risk of skin cancer and early skin aging. This product has been shown only to prevent sunburn, not skin cancer or early skin aging.

For external use only

Do not use

on damaged or broken skin

When using this product

keep out of eyes. Rinse with water to remove.

Stop use and ask a doctor

if rash occurs

Keep out of reach of children.

If swallowed, get medical help or contact a Poison Control Center right away.

Directions

- apply liberally 15 minutes before sun exposure
- reapply:
  • after 40 minutes of swimming or sweating
  • immediately after towel drying
  • at least every 2 hours
- Sun Protection Measures. Spending time in the sun increases your risk of skin cancer and early skin aging. To decrease this risk, regularly use a sunscreen with a Broad Spectrum SPF of 15 or higher and other sun protection measures including:
  • limit time in the sun, especially from 10 a.m. - 2 p.m.
  • wear long-sleeve shirts, pants, hats, and sunglasses
- children under 6 months: Ask a doctor

Inactive Ingredients

Acrylates Copolymer, Acrylates/C10-30 Alkyl Acrylate Crosspolymer, Aloe Barbadensis Leaf Extract, Carbomer, C12-15 Alkyl Benzoate, Daucus Carota Sativa (Carrot) Root Extract, Disodium EDTA, Ethylhexyl Palmitate, Ethylhexyl-glycerin, Fragrance, Glycerin, Glycine Soja (Soybean) Oil, Hydroxypropyl Methylcellulose, Phenoxyethanol, Propylene Glycol, Sorbitan Oleate, Theobroma Cacao (Cocoa) Seed Butter, Tocopheryl (Vitamin E) Acetate, Triethanolamine, Water

Other Information

- for use on skin only. Avoid contact with fabric
- protect this product from excessive heat and direct sun

Questions or comments?

www.no-ad.com or call toll free 1-800-715-3485

PRINCIPAL DISPLAY PANEL

NO-AD
SUN CARE
8
paraben free
16 FL OZ (475 mL)